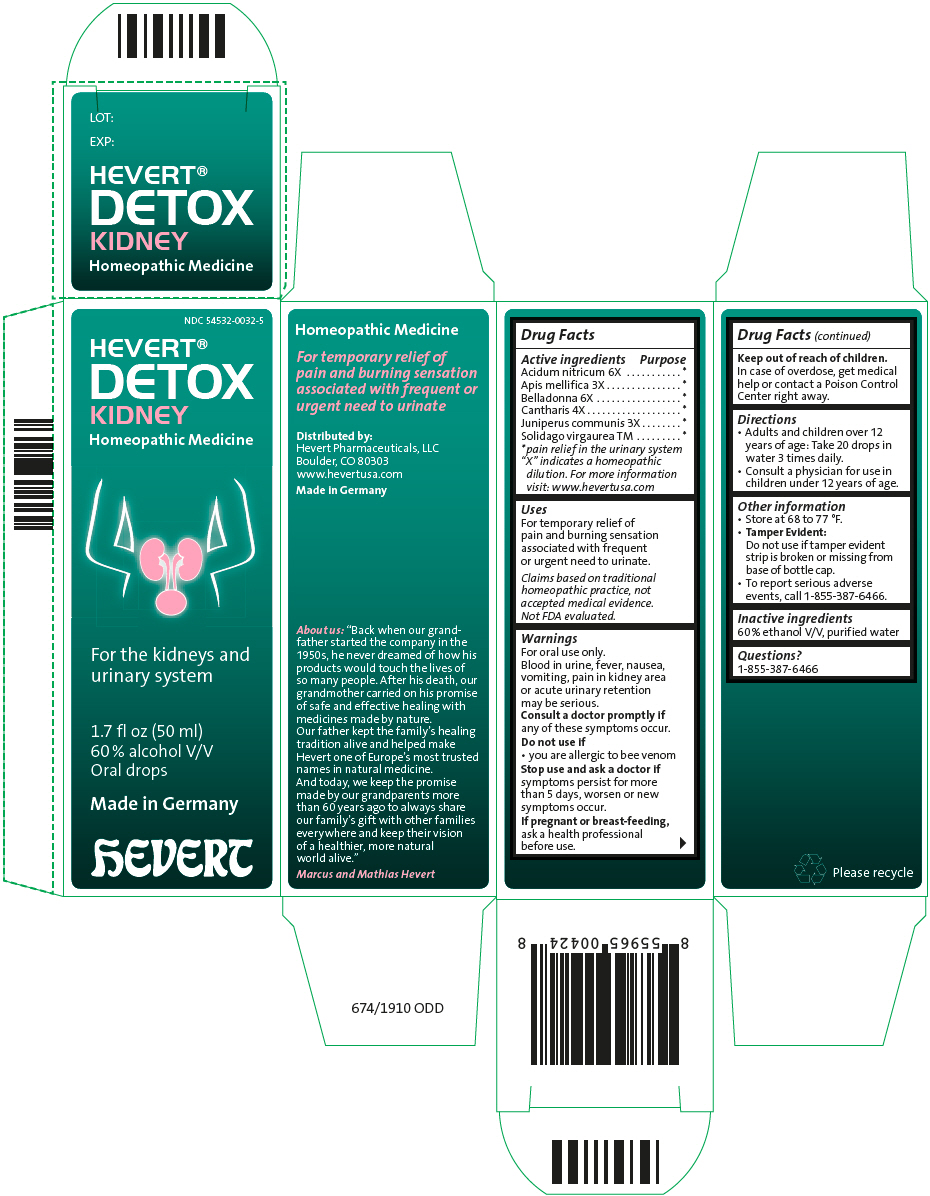 DRUG LABEL: Hevert Detox Kidney
NDC: 54532-0032 | Form: LIQUID
Manufacturer: Hevert Arzneimittel GmbH & Co KG
Category: homeopathic | Type: HUMAN OTC DRUG LABEL
Date: 20221201

ACTIVE INGREDIENTS: Nitric Acid 6 [hp_X]/50 mL; Apis Mellifera 3 [hp_X]/50 mL; Atropa Belladonna 6 [hp_X]/50 mL; Lytta Vesicatoria 4 [hp_X]/50 mL; Juniper Berry 3 [hp_X]/50 mL; Solidago Virgaurea Flowering Top 1 [hp_X]/50 mL
INACTIVE INGREDIENTS: ALCOHOL; WATER

Hevert® Detox Kidney

Drug Facts

ACTIVE INGREDIENT

PURPOSE

Active ingredients

Purpose

Acidum nitricum 6X

[pain relief in the urinary system]

Apis mellifica 3X

Belladonna 6X

Cantharis 4X

Juniperus communis 3X

Solidago virgaurea TM

"X" indicates a homeopathic dilution. For more information visit: www.hevertusa.com

Uses

For temporary relief of pain and burning sensation associated with frequent or urgent need to urinate.

Claims based on traditional homeopathic practice, not accepted medical evidence. Not FDA evaluated.

Warnings

For oral use only.

Blood in urine, fever, nausea, vomiting, pain in kidney area or acute urinary retention may be serious.

ASK DOCTOR

Consult a doctor promptly if any of these symptoms occur.

Do not use if

- you are allergic to bee venom

Stop use and ask a doctor if symptoms persist for more than 5 days, worsen or new symptoms occur.

PREGNANCY OR BREAST FEEDING

If pregnant or breast-feeding, ask a health professional before use.

Keep out of reach of children.

In case of overdose, get medical help or contact a Poison Control Center right away.

Directions

- Adults and children over 12 years of age: Take 20 drops in water 3 times daily.
- Consult a physician for use in children under 12 years of age.

Other information

- Store at 68 to 77 °F.
- Tamper Evident:
  Do not use if tamper evident strip is broken or missing from base of bottle cap.
- To report serious adverse events, call 1-855-387-6466.

Inactive ingredients

60 % ethanol V/V, purified water

Questions?

1-855-387-6466

Distributed by:
Hevert Pharmaceuticals, LLC
Boulder, CO 80303

PRINCIPAL DISPLAY PANEL - 50 mL Bottle Carton

NDC 54532-0032-5

HEVERT®
DETOX
KIDNEY

Homeopathic Medicine

For the kidneys and
urinary system

1.7 fl oz (50 ml)
60 % alcohol V/V
Oral drops

Made in Germany

hEVERT